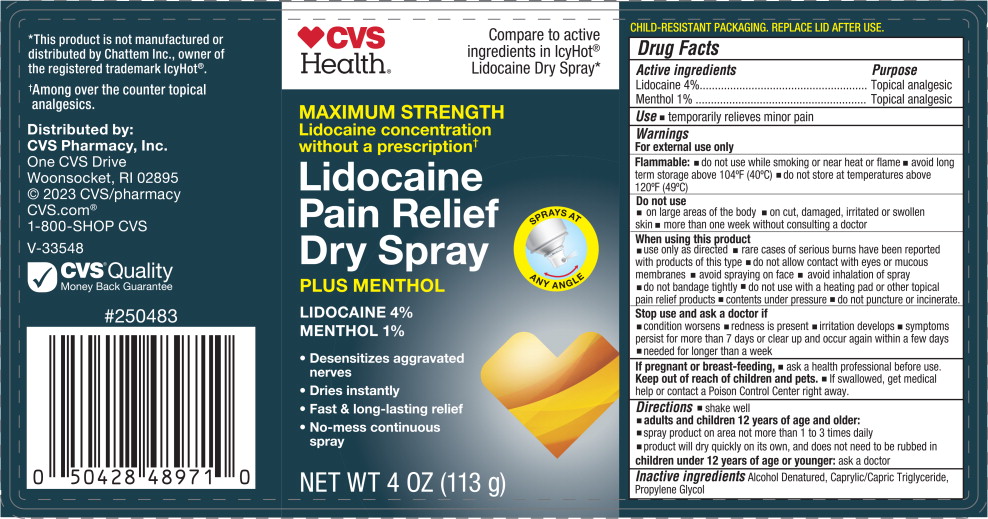 DRUG LABEL: CVS Lidocaine Pain Relief Dry
NDC: 66902-257 | Form: SPRAY
Manufacturer: Natural Essentials, Inc.
Category: otc | Type: HUMAN OTC DRUG LABEL
Date: 20241003

ACTIVE INGREDIENTS: MENTHOL, UNSPECIFIED FORM 10 mg/1 g; LIDOCAINE 40 mg/1 g
INACTIVE INGREDIENTS: ALCOHOL; MEDIUM-CHAIN TRIGLYCERIDES; PROPYLENE GLYCOL

Drug Facts

Active ingredients

Lidocaine 4%

Menthol 1%

Purpose

Topical analgesic

Topical analgesic

Use

- temporarily relieves minor pain

Warnings

For external use only

Flammable:

- do not use while smoking or near heat or flame
- avoid long term storage above 104°F (40°C)
- do not store at temperatures above 120°F(49°C)

Do not use

- on large areas of the body
- on cut, damaged, irritated or swollen skin
- more than one week without consulting a doctor

When using this product

- use only as directed
- rare cases of serious burns have been reported with products of this type
- do not allow contact with eyes or mucous membranes
- avoid spraying on face
- avoid inhalation of spray
- do not bandage tightly
- do not use with a heating pad or other topical pain relief products
- contents under pressure
- do not puncture or incinerate.

Stop use and ask a doctor if

- condition worsens
- redness is present
- irritation develops
- symptoms persist for more than 7 days or clear up and occur again within a few days
- needed for longer than a week

If pregnant or breast-feeding,

- ask a health professional before use.

Keep out of reach of children and pets.

- If swallowed, get medical help or contact a Poison Control Center right away.

Directions

- shake well
- adults and children 12 years of age and older:
- spray product on area not more than 1 to 3 times daily
- product will dry quickly on its own, and does not need to be rubbed in

children under 12 years of age or younger:ask a doctor

Inactive ingredients

Alcohol Denatured, Caprylic/Capric Triglyceride, Propylene Glycol

Principal Display Panel – 113 g Can Label

CVS
Health®

Compare to active
ingredients in IcyHot®
Lidocaine Dry Spray*

MAXIMUM STRENGTH

Lidocaine concentration
without a prescription ✝

Lidocaine
Pain Relief
Dry Spray

PLUS MENTHOL

LIDOCAINE 4%
MENTHOL 1%

- Desensitizes aggravated
  nerves
- Dries instantly
- Fast & long-lasting relief
- No-mess continuous
  spray

SPRAYS AT
ANY ANGLE

NET WT 4 0Z (113 g)